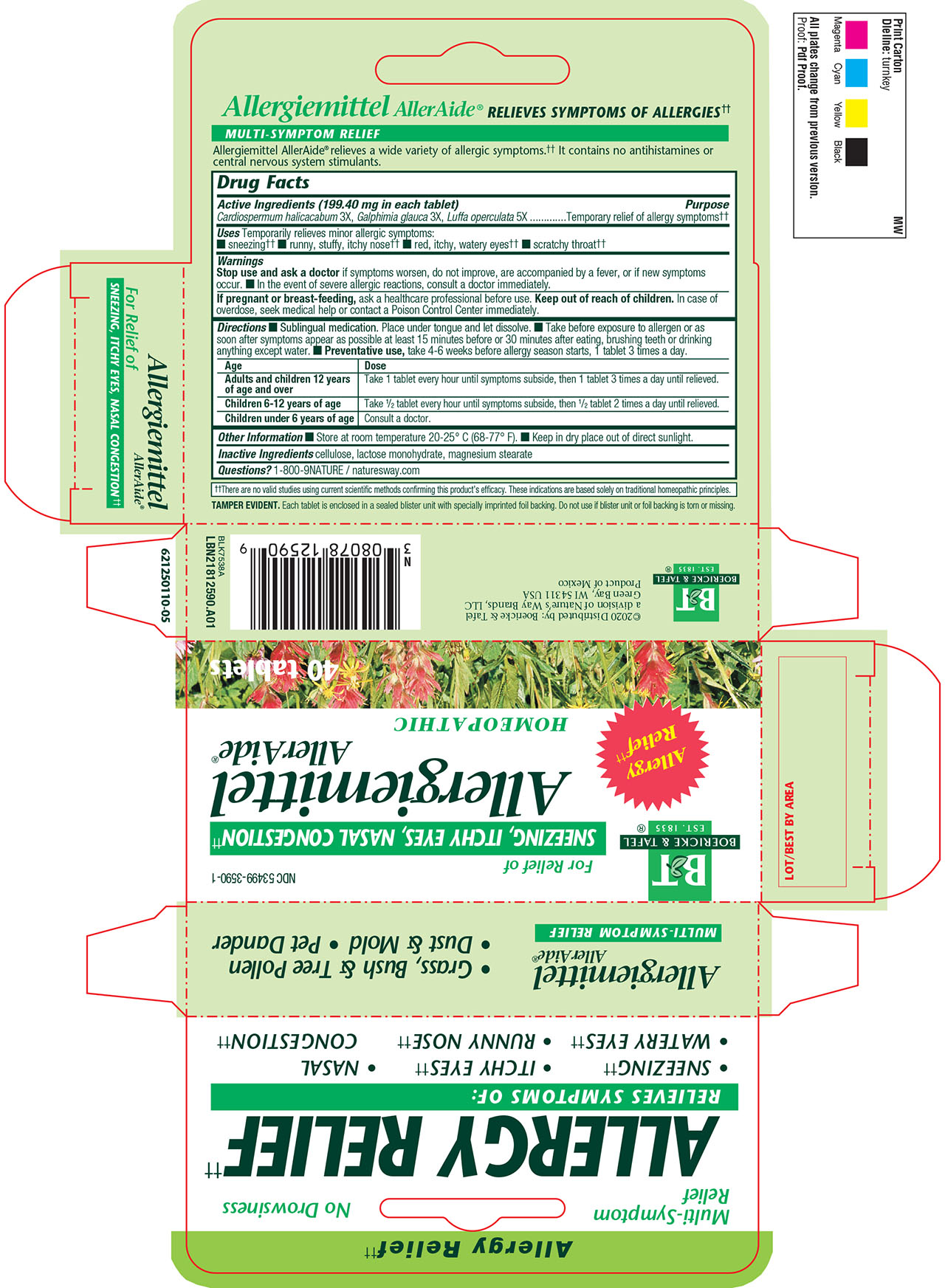 DRUG LABEL: Allergiemittel
NDC: 53499-3590 | Form: TABLET
Manufacturer: Schwabe North America, Inc.
Category: homeopathic | Type: HUMAN OTC DRUG LABEL
Date: 20251125

ACTIVE INGREDIENTS: CARDIOSPERMUM HALICACABUM FLOWERING TOP 3 [hp_X]/1 1; GALPHIMIA GLAUCA FLOWERING TOP 3 [hp_X]/1 1; LUFFA OPERCULATA FRUIT 5 [hp_X]/1 1
INACTIVE INGREDIENTS: LACTOSE MONOHYDRATE; MAGNESIUM STEARATE; CELLULOSE, MICROCRYSTALLINE

Allergiemittel Tablets

Active Ingredients

Cardiospermum halicacabum 3X

Galphimia glauca 3X

Luffa operculata 5X

Inactive Ingredients

Cellulose

Lactose Monohydrate

Magnesium Stearate

Purpose

Temporarily relieves minor allergic symptoms: sneezing, runny, stuffy, itchy nose, red, itchy, watery eyes, scratchy throat.

Indications and Usage

Temporarily relieves minor allergic symptoms: sneezing; runny, stuffy, itchy nose, red, itchy, watery eyes, scratchy throat.

Dosage & Administration

Directions:

Sublingual medication. Place under tongue and let dissolve.

Take before exposure to allergen or as soon after symptoms appear as possible at least 15 minutes before or 30 minutes after eating, brushing teeth, or drinking anything except water.

Preventative use, take 4-6 weeks before allergy season starts, 1 tablet 3 times a day.

Adults and children 12 years of age and older: Take 1 tablet every hour until symptoms subside, then 1 tablet 3 times a day until relieved.
Children 6-12 years of age: Take 1/2 tablet every hour until symptoms subside, then 1/2 tablet 2 times a day until relieved.
Children under 6 years of age: Consult a doctor.

Warnings

Stop use and ask a doctor if symptoms worsen, do not improve, are accompanied by a fever, or if new symptoms occur.

In the event of severe allergic reactions, consult a doctor immediately.

Pregnancy or Breast Feeding

If pregnant or breast-feeding, ask a healthcare professional before use.

Keep out of reach of children

Overdose

In case of overdose, seek medical help or contact a Poison Control Center immediately.